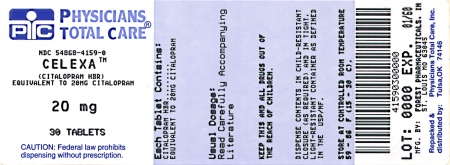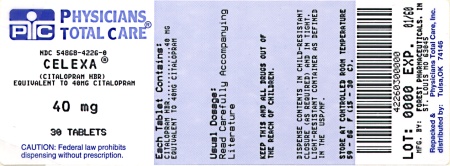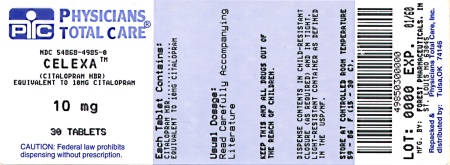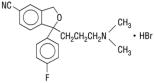 DRUG LABEL: Celexa
NDC: 54868-4985 | Form: TABLET
Manufacturer: Physicians Total Care, Inc.
Category: prescription | Type: HUMAN PRESCRIPTION DRUG LABEL
Date: 20101209

ACTIVE INGREDIENTS: CITALOPRAM HYDROBROMIDE 10 mg/1 1
INACTIVE INGREDIENTS: STARCH, CORN; CROSCARMELLOSE SODIUM; GLYCERIN; LACTOSE MONOHYDRATE; MAGNESIUM STEARATE; HYPROMELLOSES; CELLULOSE, MICROCRYSTALLINE; POLYETHYLENE GLYCOL; TITANIUM DIOXIDE

BOXED WARNING

Rx Only

Suicidality and Antidepressant Drugs

Antidepressants increased the risk compared to placebo of suicidal thinking and behavior (suicidality) in children, adolescents, and young adults in short-term studies of major depressive disorder (MDD) and other psychiatric disorders. Anyone considering the use of Celexa or any other antidepressant in a child, adolescent, or young adult must balance this risk with the clinical need. Short-term studies did not show an increase in the risk of suicidality with antidepressants compared to placebo in adults beyond age 24; there was a reduction in risk with antidepressants compared to placebo in adults aged 65 and older. Depression and certain other psychiatric disorders are themselves associated with increases in the risk of suicide. Patients of all ages who are started on antidepressant therapy should be monitored appropriately and observed closely for clinical worsening, suicidality, or unusual changes in behavior. Families and caregivers should be advised of the need for close observation and communication with the prescriber. Celexa is not approved for use in pediatric patients. (See WARNINGS: Clinical Worsening and Suicide Risk, PRECAUTIONS: Information for Patients, and PRECAUTIONS: Pediatric Use.)

DESCRIPTION

Celexa® (citalopram HBr) is an orally administered selective serotonin reuptake inhibitor (SSRI) with a chemical structure unrelated to that of other SSRIs or of tricyclic, tetracyclic, or other available antidepressant agents. Citalopram HBr is a racemic bicyclic phthalane derivative designated (±)-1-(3-dimethylaminopropyl)-1-(4-fluorophenyl)-1,3-dihydroisobenzofuran-5-carbonitrile, HBr with the following structural formula:

The molecular formula is C20H22BrFN2O and its molecular weight is 405.35.

Citalopram HBr occurs as a fine, white to off-white powder. Citalopram HBr is sparingly soluble in water and soluble in ethanol.

Celexa (citalopram hydrobromide) is available as tablets or as an oral solution.

Celexa 10 mg tablets are film-coated, oval tablets containing citalopram HBr in strengths equivalent to 10 mg citalopram base. Celexa 20 mg and 40 mg tablets are film-coated, oval, scored tablets containing citalopram HBr in strengths equivalent to 20 mg or 40 mg citalopram base. The tablets also contain the following inactive ingredients: copolyvidone, corn starch, crosscarmellose sodium, glycerin, lactose monohydrate, magnesium stearate, hypromellose, microcrystalline cellulose, polyethylene glycol, and titanium dioxide. Iron oxides are used as coloring agents in the beige (10 mg) and pink (20 mg) tablets.

Celexa oral solution contains citalopram HBr equivalent to 2 mg/mL citalopram base. It also contains the following inactive ingredients: sorbitol, purified water, propylene glycol, methylparaben, natural peppermint flavor, and propylparaben.

CLINICAL PHARMACOLOGY

Pharmacodynamics

The mechanism of action of citalopram HBr as an antidepressant is presumed to be linked to potentiation of serotonergic activity in the central nervous system (CNS) resulting from its inhibition of CNS neuronal reuptake of serotonin (5-HT). In vitro and in vivo studies in animals suggest that citalopram is a highly selective serotonin reuptake inhibitor (SSRI) with minimal effects on norepinephrine (NE) and dopamine (DA) neuronal reuptake. Tolerance to the inhibition of 5-HT uptake is not induced by long-term (14-day) treatment of rats with citalopram. Citalopram is a racemic mixture (50/50), and the inhibition of 5-HT reuptake by citalopram is primarily due to the (S)-enantiomer.

Citalopram has no or very low affinity for 5-HT1A, 5-HT2A, dopamine D1 and D2, α1-, α2-, and β-adrenergic, histamine H1, gamma aminobutyric acid (GABA), muscarinic cholinergic, and benzodiazepine receptors. Antagonism of muscarinic, histaminergic, and adrenergic receptors has been hypothesized to be associated with various anticholinergic, sedative, and cardiovascular effects of other psychotropic drugs.

Pharmacokinetics

The single- and multiple-dose pharmacokinetics of citalopram are linear and dose-proportional in a dose range of 10-60 mg/day. Biotransformation of citalopram is mainly hepatic, with a mean terminal half-life of about 35 hours. With once daily dosing, steady state plasma concentrations are achieved within approximately one week. At steady state, the extent of accumulation of citalopram in plasma, based on the half-life, is expected to be 2.5 times the plasma concentrations observed after a single dose. The tablet and oral solution dosage forms of citalopram HBr are bioequivalent.

Absorption and Distribution

Following a single oral dose (40 mg tablet) of citalopram, peak blood levels occur at about 4 hours. The absolute bioavailability of citalopram was about 80% relative to an intravenous dose, and absorption is not affected by food. The volume of distribution of citalopram is about 12 L/kg and the binding of citalopram (CT), demethylcitalopram (DCT) and didemethylcitalopram (DDCT) to human plasma proteins is about 80%.

Metabolism and Elimination

Following intravenous administrations of citalopram, the fraction of drug recovered in the urine as citalopram and DCT was about 10% and 5%, respectively. The systemic clearance of citalopram was 330 mL/min, with approximately 20% of that due to renal clearance.

Citalopram is metabolized to demethylcitalopram (DCT), didemethylcitalopram (DDCT), citalopram-N-oxide, and a deaminated propionic acid derivative. In humans, unchanged citalopram is the predominant compound in plasma. At steady state, the concentrations of citalopram's metabolites, DCT and DDCT, in plasma are approximately one-half and one-tenth, respectively, that of the parent drug. In vitro studies show that citalopram is at least 8 times more potent than its metabolites in the inhibition of serotonin reuptake, suggesting that the metabolites evaluated do not likely contribute significantly to the antidepressant actions of citalopram.

In vitro studies using human liver microsomes indicated that CYP3A4 and CYP2C19 are the primary isozymes involved in the N-demethylation of citalopram.

Population Subgroups

Age - Citalopram pharmacokinetics in subjects ≥ 60 years of age were compared to younger subjects in two normal volunteer studies. In a single-dose study, citalopram AUC and half-life were increased in the elderly subjects by 30% and 50%, respectively, whereas in a multiple-dose study they were increased by 23% and 30%, respectively. 20 mg is the recommended dose for most elderly patients (see DOSAGE AND ADMINISTRATION).

Gender - In three pharmacokinetic studies (total N=32), citalopram AUC in women was one and a half to two times that in men. This difference was not observed in five other pharmacokinetic studies (total N=114). In clinical studies, no differences in steady state serum citalopram levels were seen between men (N=237) and women (N=388). There were no gender differences in the pharmacokinetics of DCT and DDCT. No adjustment of dosage on the basis of gender is recommended.

Reduced hepatic function - Citalopram oral clearance was reduced by 37% and half-life was doubled in patients with reduced hepatic function compared to normal subjects. 20 mg is the recommended dose for most hepatically impaired patients (see DOSAGE AND ADMINISTRATION).

Reduced renal function - In patients with mild to moderate renal function impairment, oral clearance of citalopram was reduced by 17% compared to normal subjects. No adjustment of dosage for such patients is recommended. No information is available about the pharmacokinetics of citalopram in patients with severely reduced renal function (creatinine clearance < 20 mL/min).

Drug-Drug Interactions

In vitro enzyme inhibition data did not reveal an inhibitory effect of citalopram on CYP3A4, -2C9, or -2E1, but did suggest that it is a weak inhibitor of CYP1A2, -2D6, and -2C19. Citalopram would be expected to have little inhibitory effect on in vivo metabolism mediated by these cytochromes. However, in vivo data to address this question are limited.

Since CYP3A4 and 2C19 are the primary enzymes involved in the metabolism of citalopram, it is expected that potent inhibitors of 3A4 (e.g., ketoconazole, itraconazole, and macrolide antibiotics) and potent inhibitors of CYP2C19 (e.g., omeprazole) might decrease the clearance of citalopram. However, coadministration of citalopram and the potent 3A4 inhibitor ketoconazole did not significantly affect the pharmacokinetics of citalopram. Because citalopram is metabolized by multiple enzyme systems, inhibition of a single enzyme may not appreciably decrease citalopram clearance. Citalopram steady state levels were not significantly different in poor metabolizers and extensive 2D6 metabolizers after multiple-dose administration of Celexa, suggesting that coadministration, with Celexa, of a drug that inhibits CYP2D6, is unlikely to have clinically significant effects on citalopram metabolism. See Drug Interactions under PRECAUTIONS for more detailed information on available drug interaction data.

Clinical Efficacy Trials

The efficacy of Celexa as a treatment for depression was established in two placebo-controlled studies (of 4 to 6 weeks in duration) in adult outpatients (ages 18-66) meeting DSM-III or DSM-III-R criteria for major depression. Study 1, a 6-week trial in which patients received fixed Celexa doses of 10, 20, 40, and 60 mg/day, showed that Celexa at doses of 40 and 60 mg/day was effective as measured by the Hamilton Depression Rating Scale (HAMD) total score, the HAMD depressed mood item (Item 1), the Montgomery Asberg Depression Rating Scale, and the Clinical Global Impression (CGI) Severity scale. This study showed no clear effect of the 10 and 20 mg/day doses, and the 60 mg/day dose was not more effective than the 40 mg/day dose. In study 2, a 4-week, placebo-controlled trial in depressed patients, of whom 85% met criteria for melancholia, the initial dose was 20 mg/day, followed by titration to the maximum tolerated dose or a maximum dose of 80 mg/day. Patients treated with Celexa showed significantly greater improvement than placebo patients on the HAMD total score, HAMD item 1, and the CGI Severity score. In three additional placebo-controlled depression trials, the difference in response to treatment between patients receiving Celexa and patients receiving placebo was not statistically significant, possibly due to high spontaneous response rate, smaller sample size, or, in the case of one study, too low a dose.

In two long-term studies, depressed patients who had responded to Celexa during an initial 6 or 8 weeks of acute treatment (fixed doses of 20 or 40 mg/day in one study and flexible doses of 20-60 mg/day in the second study) were randomized to continuation of Celexa or to placebo. In both studies, patients receiving continued Celexa treatment experienced significantly lower relapse rates over the subsequent 6 months compared to those receiving placebo. In the fixed-dose study, the decreased rate of depression relapse was similar in patients receiving 20 or 40 mg/day of Celexa.

Analyses of the relationship between treatment outcome and age, gender, and race did not suggest any differential responsiveness on the basis of these patient characteristics.

Comparison of Clinical Trial Results

Highly variable results have been seen in the clinical development of all antidepressant drugs. Furthermore, in those circumstances when the drugs have not been studied in the same controlled clinical trial(s), comparisons among the results of studies evaluating the effectiveness of different antidepressant drug products are inherently unreliable. Because conditions of testing (e.g., patient samples, investigators, doses of the treatments administered and compared, outcome measures, etc.) vary among trials, it is virtually impossible to distinguish a difference in drug effect from a difference due to one of the confounding factors just enumerated.

INDICATIONS AND USAGE

Celexa (citalopram HBr) is indicated for the treatment of depression.

The efficacy of Celexa in the treatment of depression was established in 4-6 week, controlled trials of outpatients whose diagnosis corresponded most closely to the DSM-III and DSM-III-R category of major depressive disorder (see CLINICAL PHARMACOLOGY).

A major depressive episode (DSM-IV) implies a prominent and relatively persistent (nearly every day for at least 2 weeks) depressed or dysphoric mood that usually interferes with daily functioning, and includes at least five of the following nine symptoms: depressed mood, loss of interest in usual activities, significant change in weight and/or appetite, insomnia or hypersomnia, psychomotor agitation or retardation, increased fatigue, feelings of guilt or worthlessness, slowed thinking or impaired concentration, a suicide attempt or suicidal ideation.

The antidepressant action of Celexa in hospitalized depressed patients has not been adequately studied.

The efficacy of Celexa in maintaining an antidepressant response for up to 24 weeks following 6 to 8 weeks of acute treatment was demonstrated in two placebo-controlled trials (see CLINICAL PHARMACOLOGY). Nevertheless, the physician who elects to use Celexa for extended periods should periodically re-evaluate the long-term usefulness of the drug for the individual patient.

CONTRAINDICATIONS

Concomitant use in patients taking monoamine oxidase inhibitors (MAOIs) is contraindicated (see WARNINGS).

Concomitant use in patients taking pimozide is contraindicated (see PRECAUTIONS).

Celexa is contraindicated in patients with a hypersensitivity to citalopram or any of the inactive ingredients in Celexa.

WARNINGS

WARNINGS-Clinical Worsening and Suicide Risk Clinical Worsening and Suicide Risk

Patients with major depressive disorder (MDD), both adult and pediatric, may experience worsening of their depression and/or the emergence of suicidal ideation and behavior (suicidality) or unusual changes in behavior, whether or not they are taking antidepressant medications, and this risk may persist until significant remission occurs. Suicide is a known risk of depression and certain other psychiatric disorders, and these disorders themselves are the strongest predictors of suicide. There has been a long-standing concern, however, that antidepressants may have a role in inducing worsening of depression and the emergence of suicidality in certain patients during the early phases of treatment.

Pooled analyses of short-term placebo-controlled trials of antidepressant drugs (SSRIs and others) showed that these drugs increase the risk of suicidal thinking and behavior (suicidality) in children, adolescents, and young adults (ages 18-24) with major depressive disorder (MDD) and other psychiatric disorders. Short-term studies did not show an increase in the risk of suicidality with antidepressants compared to placebo in adults beyond age 24; there was a reduction with antidepressants compared to placebo in adults aged 65 and older.

The pooled analyses of placebo-controlled trials in children and adolescents with MDD, obsessive compulsive disorder (OCD), or other psychiatric disorders included a total of 24 short-term trials of 9 antidepressant drugs in over 4400 patients. The pooled analyses of placebo-controlled trials in adults with MDD or other psychiatric disorders included a total of 295 short-term trials (median duration of 2 months) of 11 antidepressant drugs in over 77,000 patients. There was considerable variation in risk of suicidality among drugs, but a tendency toward an increase in the younger patients for almost all drugs studied. There were differences in absolute risk of suicidality across the different indications, with the highest incidence in MDD. The risk differences (drug vs. placebo), however, were relatively stable within age strata and across indications. These risk differences (drug-placebo difference in the number of cases of suicidality per 1000 patients treated) are provided in Table 1.

TABLE 1
Age Range | Drug-Placebo Difference in Number of Cases of Suicidality per 1000 Patients Treated
 | Increases Compared to Placebo
<18 | 14 additional cases
18-24 | 5 additional cases
 | Decreases Compared to Placebo
25-64 | 1 fewer case
>65 | 6 fewer cases

No suicides occurred in any of the pediatric trials. There were suicides in the adult trials, but the number was not sufficient to reach any conclusion about drug effect on suicide.

It is unknown whether the suicidality risk extends to longer-term use, i.e., beyond several months. However, there is substantial evidence from placebo-controlled maintenance trials in adults with depression that the use of antidepressants can delay the recurrence of depression.

All patients being treated with antidepressants for any indication should be monitored appropriately and observed closely for clinical worsening, suicidality, and unusual changes in behavior, especially during the initial few months of a course of drug therapy, or at times of dose changes, either increases or decreases.

The following symptoms, anxiety, agitation, panic attacks, insomnia, irritability, hostility, aggressiveness, impulsivity, akathisia (psychomotor restlessness), hypomania, and mania, have been reported in adult and pediatric patients being treated with antidepressants for major depressive disorder as well as for other indications, both psychiatric and nonpsychiatric. Although a causal link between the emergence of such symptoms and either the worsening of depression and/or the emergence of suicidal impulses has not been established, there is concern that such symptoms may represent precursors to emerging suicidality.

Consideration should be given to changing the therapeutic regimen, including possibly discontinuing the medication, in patients whose depression is persistently worse, or who are experiencing emergent suicidality or symptoms that might be precursors to worsening depression or suicidality, especially if these symptoms are severe, abrupt in onset, or were not part of the patient's presenting symptoms.

If the decision has been made to discontinue treatment, medication should be tapered, as rapidly as is feasible, but with recognition that abrupt discontinuation can be associated with certain symptoms (see PRECAUTIONS and DOSAGE AND ADMINISTRATION—Discontinuation of Treatment with Celexa, for a description of the risks of discontinuation of Celexa.

Families and caregivers of patients being treated with antidepressants for major depressive disorder or other indications, both psychiatric and nonpsychiatric, should be alerted about the need to monitor patients for the emergence of agitation, irritability, unusual changes in behavior, and the other symptoms described above, as well as the emergence of suicidality, and to report such symptoms immediately to health care providers. Such monitoring should include daily observation by families and caregivers. Prescriptions for Celexa should be written for the smallest quantity of tablets consistent with good patient management, in order to reduce the risk of overdose.

Screening Patients for Bipolar Disorder: A major depressive episode may be the initial presentation of bipolar disorder. It is generally believed (though not established in controlled trials) that treating such an episode with an antidepressant alone may increase the likelihood of precipitation of a mixed/manic episode in patients at risk for bipolar disorder. Whether any of the symptoms described above represent such a conversion is unknown. However, prior to initiating treatment with an antidepressant, patients with depressive symptoms should be adequately screened to determine if they are at risk for bipolar disorder; such screening should include a detailed psychiatric history, including a family history of suicide, bipolar disorder, and depression. It should be noted that Celexa is not approved for use in treating bipolar depression.

Potential for Interaction with Monoamine Oxidase Inhibitors

In patients receiving serotonin reuptake inhibitor drugs in combination with a monoamine oxidase inhibitor (MAOI), there have been reports of serious, sometimes fatal, reactions including hyperthermia, rigidity, myoclonus, autonomic instability with possible rapid fluctuations of vital signs, and mental status changes that include extreme agitation progressing to delirium and coma. These reactions have also been reported in patients who have recently discontinued SSRI treatment and have been started on an MAOI. Some cases presented with features resembling neuroleptic malignant syndrome. Furthermore, limited animal data on the effects of combined use of SSRIs and MAOIs suggest that these drugs may act synergistically to elevate blood pressure and evoke behavioral excitation. Therefore, it is recommended that Celexa should not be used in combination with an MAOI, or within 14 days of discontinuing treatment with an MAOI. Similarly, at least 14 days should be allowed after stopping Celexa before starting an MAOI.

Serotonin Syndrome or Neuroleptic Malignant Syndrome (NMS)-like Reactions

The development of a potentially life-threatening serotonin syndrome or Neuroleptic Malignant Syndrome (NMS)-like reactions have been reported with SNRIs and SSRIs alone, including Celexa treatment, but particularly with concomitant use of serotonergic drugs (including triptans) with drugs which impair metabolism of serotonin (including MAOIs), or with antipsychotics or other dopamine antagonists. Serotonin syndrome symptoms may include mental status changes (e.g., agitation, hallucinations, coma), autonomic instability (e.g., tachycardia, labile blood pressure, hyperthermia), neuromuscular aberrations (e.g., hyperreflexia, incoordination) and/or gastrointestinal symptoms (e.g., nausea, vomiting, diarrhea). Serotonin syndrome, in its most severe form can resemble neuroleptic malignant syndrome, which includes hyperthermia, muscle rigidity, autonomic instability with possible rapid fluctuation of vital signs, and mental status changes. Patients should be monitored for the emergence of serotonin syndrome or NMS-like signs and symptoms.

The concomitant use of Celexa with MAOIs intended to treat depression is contraindicated. If concomitant treatment of Celexa with a 5-hydroxytryptamine receptor agonist (triptan) is clinically warranted, careful observation of the patient is advised, particularly during treatment initiation and dose increases.

The concomitant use of Celexa with serotonin precursors (such as tryptophan) is not recommended. Treatment with Celexa and any concomitant serotonergic or antidopaminergic agents, including antipsychotics, should be discontinued immediately if the above events occur and supportive symptomatic treatment should be initiated.

PRECAUTIONS

General Discontinuation of Treatment with Celexa

During marketing of Celexa and other SSRIs and SNRIs (serotonin and norepinephrine reuptake inhibitors), there have been spontaneous reports of adverse events occurring upon discontinuation of these drugs, particularly when abrupt, including the following: dysphoric mood, irritability, agitation, dizziness, sensory disturbances (e.g., paresthesias such as electric shock sensations), anxiety, confusion, headache, lethargy, emotional lability, insomnia, and hypomania. While these events are generally self-limiting, there have been reports of serious discontinuation symptoms.

Patients should be monitored for these symptoms when discontinuing treatment with Celexa. A gradual reduction in the dose rather than abrupt cessation is recommended whenever possible. If intolerable symptoms occur following a decrease in the dose or upon discontinuation of treatment, then resuming the previously prescribed dose may be considered. Subsequently, the physician may continue decreasing the dose but at a more gradual rate (see DOSAGE AND ADMINISTRATION).

Abnormal Bleeding

SSRIs and SNRIs, including Lexapro, may increase the risk of bleeding events. Concomitant use of aspirin, nonsteroidal anti-inflammatory drugs, warfarin, and other anticoagulants may add to the risk. Case reports and epidemiological studies (case-control and cohort design) have demonstrated an association between use of drugs that interfere with serotonin reuptake and the occurrence of gastrointestinal bleeding. Bleeding events related to SSRIs and SNRIs use have ranged from ecchymoses, hematomas, epistaxis, and petechiae to life-threatening hemorrhages.

Patients should be cautioned about the risk of bleeding associated with the concomitant use of Lexapro and NSAIDs, aspirin, or other drugs that affect coagulation.

Hyponatremia

Hyponatremia may occur as a result of treatment with SSRIs and SNRIs, including Celexa. In many cases, this hyponatremia appears to be the result of the syndrome of inappropriate antidiureic hormone secretion (SIADH), and was reversible when Celexa was discontinued. Cases with serum sodium lower than 110 mmol/L have been reported. Elderly patients may be at greater risk of developing hyponatremia with SSRIs and SNRIs. Also, patients taking diuretics or who are otherwise volume depleted may be at greater risk (see Geriatric Use). Discontinuation of Celexa should be considered in patients with symptomatic hyponatremia and appropriate medical intervention should be instituted.

Signs and symptoms of hyponatremia include headache, difficulty concentrating, memory impairment, confusion, weakness, and unsteadiness, which may lead to falls. signs and symptoms associated with more severe and/or acute cases have included hallucination, syncompe, seizure, coma, respiratory arrest, and death.

Activation of Mania/Hypomania

In placebo-controlled trials of Celexa, some of which included patients with bipolar disorder, activation of mania/hypomania was reported in 0.2% of 1063 patients treated with Celexa and in none of the 446 patients treated with placebo. Activation of mania/hypomania has also been reported in a small proportion of patients with major affective disorders treated with other marketed antidepressants. As with all antidepressants, Celexa should be used cautiously in patients with a history of mania.

Seizures

Although anticonvulsant effects of citalopram have been observed in animal studies, Celexa has not been systematically evaluated in patients with a seizure disorder. These patients were excluded from clinical studies during the product's premarketing testing. In clinical trials of Celexa, seizures occurred in 0.3% of patients treated with Celexa (a rate of one patient per 98 years of exposure) and 0.5% of patients treated with placebo (a rate of one patient per 50 years of exposure). Like other antidepressants, Celexa should be introduced with care in patients with a history of seizure disorder.

Interference with Cognitive and Motor Performance

In studies in normal volunteers, Celexa in doses of 40 mg/day did not produce impairment of intellectual function or psychomotor performance. Because any psychoactive drug may impair judgment, thinking, or motor skills, however, patients should be cautioned about operating hazardous machinery, including automobiles, until they are reasonably certain that Celexa therapy does not affect their ability to engage in such activities.

Use in Patients with Concomitant Illness

Clinical experience with Celexa in patients with certain concomitant systemic illnesses is limited. Caution is advisable in using Celexa in patients with diseases or conditions that produce altered metabolism or hemodynamic responses.

Celexa has not been systematically evaluated in patients with a recent history of myocardial infarction or unstable heart disease. Patients with these diagnoses were generally excluded from clinical studies during the product's premarketing testing. However, the electrocardiograms of 1116 patients who received Celexa in clinical trials were evaluated and the data indicate that Celexa is not associated with the development of clinically significant ECG abnormalities.

In subjects with hepatic impairment, citalopram clearance was decreased and plasma concentrations were increased. The use of Celexa in hepatically impaired patients should be approached with caution and a lower maximum dosage is recommended (see DOSAGE AND ADMINISTRATION).

Because citalopram is extensively metabolized, excretion of unchanged drug in urine is a minor route of elimination. Until adequate numbers of patients with severe renal impairment have been evaluated during chronic treatment with Celexa, however, it should be used with caution in such patients (see DOSAGE AND ADMINISTRATION).

Information for Patients

Physicians are advised to discuss the following issues with patients for whom they prescribe Celexa.

Patients should be cautioned about the risk of serotonin syndrome with the concomitant use of Celexa and triptans, tramadol or other serotonergic agents.

Although in controlled studies Celexa has not been shown to impair psychomotor performance, any psychoactive drug may impair judgment, thinking, or motor skills, so patients should be cautioned about operating hazardous machinery, including automobiles, until they are reasonably certain that Celexa therapy does not affect their ability to engage in such activities.

Patients should be told that, although Celexa has not been shown in experiments with normal subjects to increase the mental and motor skill impairments caused by alcohol, the concomitant use of Celexa and alcohol in depressed patients is not advised.

Patients should be advised to inform their physician if they are taking, or plan to take, any prescription or over-the-counter drugs, as there is a potential for interactions.

Patients should be cautioned about the concomitant use of Celexa and NSAIDs, aspirin, warfarin, or other drugs that affect coagulation since combined use of psychotropic drugs that interfere with serotonin reuptake and these agents has been associated with an increased risk of bleeding.

Patients should be advised to notify their physician if they become pregnant or intend to become pregnant during therapy.

Patients should be advised to notify their physician if they are breastfeeding an infant.

While patients may notice improvement with Celexa therapy in 1 to 4 weeks, they should be advised to continue therapy as directed.

Prescribers or other health professionals should inform patients, their families, and their caregivers about the benefits and risks associated with treatment with Celexa and should counsel them in its appropriate use. A patient Medication Guide about “Antidepressant Medicines, Depression and other Serious Mental Illness, and Suicidal Thoughts or Actions” is available for Celexa. The prescriber or health professional should instruct patients, their families, and their caregivers to read the Medication Guide and should assist them in understanding its contents. Patients should be given the opportunity to discuss the contents of the Medication Guide and to obtain answers to any questions they may have. The complete text of the Medication Guide is reprinted at the end of this document.

Patients should be advised of the following issues and asked to alert their prescriber if these occur while taking Celexa.

Clinical Worsening and Suicide Risk: Patients, their families, and their caregivers should be encouraged to be alert to the emergence of anxiety, agitation, panic attacks, insomnia, irritability, hostility, aggressiveness, impulsivity, akathisia (psychomotor restlessness), hypomania, mania, other unusual changes in behavior, worsening of depression, and suicidal ideation, especially early during antidepressant treatment and when the dose is adjusted up or down. Families and caregivers of patients should be advised to look for the emergence of such symptoms on a day-to-day basis, since changes may be abrupt. Such symptoms should be reported to the patient's prescriber or health professional, especially if they are severe, abrupt in onset, or were not part of the patient's presenting symptoms. Symptoms such as these may be associated with an increased risk for suicidal thinking and behavior and indicate a need for very close monitoring and possibly changes in the medication.

Laboratory Tests

There are no specific laboratory tests recommended.

Drug Interactions

Serotonergic Drugs: Based on the mechanism of action of SNRIs and SSRIs including Celexa, and the potential for serotonin syndrome, caution is advised when Celexa is coadministered with other drugs that may affect the serotonergic neurotransmitter systems, such as triptans, linezolid (an antibiotic which is a reversible non-selective MAOI), lithium, tramadol, or St. John's Wort (see WARNINGS-Serotonin Syndrome). The concomitant use of Celexa with other SSRIs, SNRIs or tryptophan is not recommended (see PRECAUTIONS - Drug Interactions).

Triptans: There have been rare postmarketing reports of serotonin syndrome with use of an SSRI and a triptan. If concomitant treatment of Celexa with a triptan is clinically warranted, careful observation of the patient is advised, particularly during treatment initiation and dose increases (see WARNINGS - Serotonin Syndrome).

CNS Drugs - Given the primary CNS effects of citalopram, caution should be used when it is taken in combination with other centrally acting drugs.

Alcohol - Although citalopram did not potentiate the cognitive and motor effects of alcohol in a clinical trial, as with other psychotropic medications, the use of alcohol by depressed patients taking Celexa is not recommended.

Monoamine Oxidase Inhibitors (MAOIs) - See CONTRAINDICATIONS and WARNINGS.

Drugs That Interfere With Hemostasis (NSAIDs, Aspirin, Warfarin, etc.)- Serotonin release by platelets plays an important role in hemostasis. Epidemiological studies of the case-control and cohort design that have demonstrated an association between use of psychotropic drugs that interfere with serotonin reuptake and the occurrence of upper gastrointestinal bleeding. These studies have also shown that concurrent use of an NSAID or aspirin may potentiate the risk of bleeding.

Altered anticoagulant effects, including increased bleeding, have been reported when SSRIs and SNRIs are coadministered with warfarin. Patients receiving warfarin therapy should be carefully monitored when Lexapro is initiated or discontinued.

Cimetidine - In subjects who had received 21 days of 40 mg/day Celexa, combined administration of 400 mg/day cimetidine for 8 days resulted in an increase in citalopram AUC and Cmax of 43% and 39%, respectively. The clinical significance of these findings is unknown.

Digoxin - In subjects who had received 21 days of 40 mg/day Celexa, combined administration of Celexa and digoxin (single dose of 1 mg) did not significantly affect the pharmacokinetics of either citalopram or digoxin.

Lithium - Coadministration of Celexa (40 mg/day for 10 days) and lithium (30 mmol/day for 5 days) had no significant effect on the pharmacokinetics of citalopram or lithium. Nevertheless, plasma lithium levels should be monitored with appropriate adjustment to the lithium dose in accordance with standard clinical practice. Because lithium may enhance the serotonergic effects of citalopram, caution should be exercised when Celexa and lithium are coadministered.

Pimozide - In a controlled study, a single dose of pimozide 2 mg co-administered with citalopram 40 mg given once daily for 11 days was associated with a mean increase in QTc values of approximately 10 msec compared to pimozide given alone. Citalopram did not alter the mean AUC or Cmax of pimozide. The mechanism of this pharmacodynamic interaction is not known.

Theophylline - Combined administration of Celexa (40 mg/day for 21 days) and the CYP1A2 substrate theophylline (single dose of 300 mg) did not affect the pharmacokinetics of theophylline. The effect of theophylline on the pharmacokinetics of citalopram was not evaluated.

Sumatriptan - There have been rare postmarketing reports describing patients with weakness, hyperreflexia, and incoordination following the use of a SSRI and sumatriptan. If concomitant treatment with sumatriptan and an SSRI (e.g., fluoxetine, fluvoxamine, paroxetine, sertraline, citalopram) is clinically warranted, appropriate observation of the patient is advised.

Warfarin - Administration of 40 mg/day Celexa for 21 days did not affect the pharmacokinetics of warfarin, a CYP3A4 substrate. Prothrombin time was increased by 5%, the clinical significance of which is unknown.

Carbamazepine - Combined administration of Celexa (40 mg/day for 14 days) and carbamazepine (titrated to 400 mg/day for 35 days) did not significantly affect the pharmacokinetics of carbamazepine, a CYP3A4 substrate. Although trough citalopram plasma levels were unaffected, given the enzyme-inducing properties of carbamazepine, the possibility that carbamazepine might increase the clearance of citalopram should be considered if the two drugs are coadministered.

Triazolam - Combined administration of Celexa (titrated to 40 mg/day for 28 days) and the CYP3A4 substrate triazolam (single dose of 0.25 mg) did not significantly affect the pharmacokinetics of either citalopram or triazolam.

Ketoconazole - Combined administration of Celexa (40 mg) and ketoconazole (200 mg) decreased the Cmax and AUC of ketoconazole by 21% and 10%, respectively, and did not significantly affect the pharmacokinetics of citalopram.

CYP3A4 and 2C19 Inhibitors - In vitro studies indicated that CYP3A4 and 2C19 are the primary enzymes involved in the metabolism of citalopram. However, coadministration of citalopram (40 mg) and ketoconazole (200 mg), a potent inhibitor of CYP3A4, did not significantly affect the pharmacokinetics of citalopram. Because citalopram is metabolized by multiple enzyme systems, inhibition of a single enzyme may not appreciably decrease citalopram clearance.

Metoprolol - Administration of 40 mg/day Celexa for 22 days resulted in a two-fold increase in the plasma levels of the beta-adrenergic blocker metoprolol. Increased metoprolol plasma levels have been associated with decreased cardioselectivity. Coadministration of Celexa and metoprolol had no clinically significant effects on blood pressure or heart rate.

Imipramine and Other Tricyclic Antidepressants (TCAs) - In vitro studies suggest that citalopram is a relatively weak inhibitor of CYP2D6. Coadministration of Celexa (40 mg/day for 10 days) with the TCA imipramine (single dose of 100 mg), a substrate for CYP2D6, did not significantly affect the plasma concentrations of imipramine or citalopram. However, the concentration of the imipramine metabolite desipramine was increased by approximately 50%. The clinical significance of the desipramine change is unknown. Nevertheless, caution is indicated in the coadministration of TCAs with Celexa.

Electroconvulsive Therapy (ECT) - There are no clinical studies of the combined use of electroconvulsive therapy (ECT) and Celexa.

Carcinogenesis, Mutagenesis, Impairment of Fertility Carcinogenesis

Citalopram was administered in the diet to NMRI/BOM strain mice and COBS WI strain rats for 18 and 24 months, respectively. There was no evidence for carcinogenicity of citalopram in mice receiving up to 240 mg/kg/day, which is equivalent to 20 times the maximum recommended human daily dose (MRHD) of 60 mg on a surface area (mg/m^2) basis. There was an increased incidence of small intestine carcinoma in rats receiving 8 or 24 mg/kg/day, doses which are approximately 1.3 and 4 times the MRHD, respectively, on a mg/m^2 basis. A no-effect dose for this finding was not established. The relevance of these findings to humans is unknown.

Mutagenesis

Citalopram was mutagenic in the in vitro bacterial reverse mutation assay (Ames test) in 2 of 5 bacterial strains (Salmonella TA98 and TA1537) in the absence of metabolic activation. It was clastogenic in the in vitro Chinese hamster lung cell assay for chromosomal aberrations in the presence and absence of metabolic activation. Citalopram was not mutagenic in the in vitro mammalian forward gene mutation assay (HPRT) in mouse lymphoma cells or in a coupled in vitro/in vivo unscheduled DNA synthesis (UDS) assay in rat liver. It was not clastogenic in the in vitro chromosomal aberration assay in human lymphocytes or in two in vivo mouse micronucleus assays.

Impairment of Fertility

When citalopram was administered orally to 16 male and 24 female rats prior to and throughout mating and gestation at doses of 32, 48, and 72 mg/kg/day, mating was decreased at all doses, and fertility was decreased at doses ≥ 32 mg/kg/day, approximately 5 times the MRHD of 60 mg/day on a body surface area (mg/m^2) basis. Gestation duration was increased at 48 mg/kg/day, approximately 8 times the MRHD.

Pregnancy Pregnancy Category C

In animal reproduction studies, citalopram has been shown to have adverse effects on embryo/fetal and postnatal development, including teratogenic effects, when administered at doses greater than human therapeutic doses.

In two rat embryo/fetal development studies, oral administration of citalopram (32, 56, or 112 mg/kg/day) to pregnant animals during the period of organogenesis resulted in decreased embryo/fetal growth and survival and an increased incidence of fetal abnormalities (including cardiovascular and skeletal defects) at the high dose, which is approximately 18 times the MRHD of 60 mg/day on a body surface area (mg/m^2) basis. This dose was also associated with maternal toxicity (clinical signs, decreased body weight gain). The developmental, no-effect dose of 56 mg/kg/day is approximately 9 times the MRHD on a mg/m^2 basis. In a rabbit study, no adverse effects on embryo/fetal development were observed at doses of up to 16 mg/kg/day, or approximately 5 times the MRHD on a mg/m^2 basis. Thus, teratogenic effects were observed at a maternally toxic dose in the rat and were not observed in the rabbit.

When female rats were treated with citalopram (4.8, 12.8, or 32 mg/kg/day) from late gestation through weaning, increased offspring mortality during the first 4 days after birth and persistent offspring growth retardation were observed at the highest dose, which is approximately 5 times the MRHD on a mg/m^2 basis. The no-effect dose of 12.8 mg/kg/day is approximately 2 times the MRHD on a mg/m^2 basis. Similar effects on offspring mortality and growth were seen when dams were treated throughout gestation and early lactation at doses ≥ 24 mg/kg/day, approximately 4 times the MRHD on a mg/m^2 basis. A no-effect dose was not determined in that study.

There are no adequate and well-controlled studies in pregnant women; therefore, citalopram should be used during pregnancy only if the potential benefit justifies the potential risk to the fetus.

Pregnancy-Nonteratogenic Effects

Neonates exposed to Celexa and other SSRIs or SNRIs, late in the third trimester, have developed complications requiring prolonged hospitalization, respiratory support, and tube feeding. Such complications can arise immediately upon delivery. Reported clinical findings have included respiratory distress, cyanosis, apnea, seizures, temperature instability, feeding difficulty, vomiting, hypoglycemia, hypotonia, hypertonia, hyperreflexia, tremor, jitteriness, irritability, and constant crying. These features are consistent with either a direct toxic effect of SSRIs and SNRIs or, possibly, a drug discontinuation syndrome. It should be noted that, in some cases, the clinical picture is consistent with serotonin syndrome (see WARNINGS).

Infants exposed to SSRIs in late pregnancy may have an increased risk for persistent pulmonary hypertension of the newborn (PPHN). PPHN occurs in 1—2 per 1000 live births in the general population and is associated with substantial neonatal morbidity and mortality. In a retrospective, case-control study of 377 women whose infants were born with PPHN and 836 women whose infants were born healthy, the risk for developing PPHN was approximately six-fold higher for infants exposed to SSRIs after the 20th week of gestation compared to infants who had not been exposed to antidepressants during pregnancy. There is currently no corroborative evidence regarding the risk for PPHN following exposure to SSRIs in pregnancy; this is the first study that has investigated the potential risk. The study did not include enough cases with exposure to individual SSRIs to determine if all SSRIs posed similar levels of PPHN risk.

When treating a pregnant woman with Celexa during the third trimester, the physician should carefully consider both the potential risks and benefits of treatment (see DOSAGE AND ADMINISTRATION). Physicians should note that in a prospective longitudinal study of 201 women with a history of major depression who were euthymic at the beginning of pregnancy, women who discontinued antidepressant medication during pregnancy were more likely to experience a relapse of major depression than women who continued antidepressant medication.

Labor and Delivery

The effect of Celexa on labor and delivery in humans is unknown.

Nursing Mothers

As has been found to occur with many other drugs, citalopram is excreted in human breast milk. There have been two reports of infants experiencing excessive somnolence, decreased feeding, and weight loss in association with breastfeeding from a citalopram-treated mother; in one case, the infant was reported to recover completely upon discontinuation of citalopram by its mother and in the second case, no follow-up information was available. The decision whether to continue or discontinue either nursing or Celexa therapy should take into account the risks of citalopram exposure for the infant and the benefits of Celexa treatment for the mother.

Pediatric Use

Safety and effectiveness in the pediatric population have not been established (see BOX WARNING and WARNINGS—Clinical Worsening and Suicide Risk). Two placebo-controlled trials in 407 pediatric patients with MDD have been conducted with Celexa, and the data were not sufficient to support a claim for use in pediatric patients. Anyone considering the use of Celexa in a child or adolescent must balance the potential risks with the clinical need.

Geriatric Use

Of 4422 patients in clinical studies of Celexa, 1357 were 60 and over, 1034 were 65 and over, and 457 were 75 and over. No overall differences in safety or effectiveness were observed between these subjects and younger subjects, and other reported clinical experience has not identified differences in responses between the elderly and younger patients, but greater sensitivity of some older individuals cannot be ruled out. Most elderly patients treated with Celexa in clinical trials received daily doses between 20 and 40 mg (see DOSAGE AND ADMINISTRATION).

SSRIs and SNRIs, including Celexa, have been associated with cases of clinically significant hyponatremia in elderly patients, who may be at greater risk for this adverse event (see PRECAUTIONS, Hyponatremia).

In two pharmacokinetic studies, citalopram AUC was increased by 23% and 30%, respectively, in elderly subjects as compared to younger subjects, and its half-life was increased by 30% and 50%, respectively (see CLINICAL PHARMACOLOGY).

20 mg/day is the recommended dose for most elderly patients (see DOSAGE AND ADMINISTRATION).

ADVERSE REACTIONS

The premarketing development program for Celexa included citalopram exposures in patients and/or normal subjects from 3 different groups of studies: 429 normal subjects in clinical pharmacology/pharmacokinetic studies; 4422 exposures from patients in controlled and uncontrolled clinical trials, corresponding to approximately 1370 patient-exposure years. There were, in addition, over 19,000 exposures from mostly open-label, European postmarketing studies. The conditions and duration of treatment with Celexa varied greatly and included (in overlapping categories) open-label and double-blind studies, inpatient and outpatient studies, fixed-dose and dose-titration studies, and short-term and long-term exposure. Adverse reactions were assessed by collecting adverse events, results of physical examinations, vital signs, weights, laboratory analyses, ECGs, and results of ophthalmologic examinations.

Adverse events during exposure were obtained primarily by general inquiry and recorded by clinical investigators using terminology of their own choosing. Consequently, it is not possible to provide a meaningful estimate of the proportion of individuals experiencing adverse events without first grouping similar types of events into a smaller number of standardized event categories. In the tables and tabulations that follow, standard World Health Organization (WHO) terminology has been used to classify reported adverse events.

The stated frequencies of adverse events represent the proportion of individuals who experienced, at least once, a treatment-emergent adverse event of the type listed. An event was considered treatment-emergent if it occurred for the first time or worsened while receiving therapy following baseline evaluation.

Adverse Findings Observed in Short-Term, Placebo-Controlled Trials Adverse Events Associated with Discontinuation of Treatment

Among 1063 depressed patients who received Celexa at doses ranging from 10 to 80 mg/day in placebo-controlled trials of up to 6 weeks in duration, 16% discontinued treatment due to an adverse event, as compared to 8% of 446 patients receiving placebo. The adverse events associated with discontinuation and considered drug-related (i.e., associated with discontinuation in at least 1% of Celexa-treated patients at a rate at least twice that of placebo) are shown in TABLE 2. It should be noted that one patient can report more than one reason for discontinuation and be counted more than once in this table.

TABLE 2 Adverse Events Associated with Discontinuation of Treatment in Short-Term, Placebo-Controlled, Depression Trials
Percentage of Patients Discontinuing
Due to Adverse Event
 | Citalopram | Placebo
 | (N=1063) | (N=446)
Body System/Adverse Event
General
Asthenia | 1% | <1%
Gastrointestinal Disorders
Nausea | 4% | 0%
Dry Mouth | 1% | <1%
Vomiting | 1% | 0%
Central and Peripheral
Nervous System Disorders
Dizziness | 2% | <1%
Psychiatric Disorders
Insomnia | 3% | 1%
Somnolence | 2% | 1%
Agitation | 1% | <1%

Adverse Events Occurring at an Incidence of 2% or More Among Celexa -Treated Patients

Table 3 enumerates the incidence, rounded to the nearest percent, of treatment-emergent adverse events that occurred among 1063 depressed patients who received Celexa at doses ranging from 10 to 80 mg/day in placebo-controlled trials of up to 6 weeks in duration. Events included are those occurring in 2% or more of patients treated with Celexa and for which the incidence in patients treated with Celexa was greater than the incidence in placebo-treated patients.

The prescriber should be aware that these figures cannot be used to predict the incidence of adverse events in the course of usual medical practice where patient characteristics and other factors differ from those which prevailed in the clinical trials. Similarly, the cited frequencies cannot be compared with figures obtained from other clinical investigations involving different treatments, uses, and investigators. The cited figures, however, do provide the prescribing physician with some basis for estimating the relative contribution of drug and non-drug factors to the adverse event incidence rate in the population studied.

The only commonly observed adverse event that occurred in Celexa patients with an incidence of 5% or greater and at least twice the incidence in placebo patients was ejaculation disorder (primarily ejaculatory delay) in male patients (see TABLE 3).

TABLE 3 Treatment-Emergent Adverse Events: Incidence in Placebo-Controlled Clinical Trials*
(Percentage of Patients Reporting Event)
Body System/Adverse Event | Celexa | Placebo
 | (N=1063) | (N=446)
Autonomic Nervous System
Disorders
Dry Mouth | 20% | 14%
Sweating Increased | 11% | 9%
Central & Peripheral Nervous
System Disorders
Tremor | 8% | 6%
Gastrointestinal Disorders
Nausea | 21% | 14%
Diarrhea | 8% | 5%
Dyspepsia | 5% | 4%
Vomiting | 4% | 3%
Abdominal Pain | 3% | 2%
General
Fatigue | 5% | 3%
Fever | 2% | <1%
Musculoskeletal System
Disorders
Arthralgia | 2% | 1%
Myalgia | 2% | 1%
Psychiatric Disorders
Somnolence | 18% | 10%
Insomnia | 15% | 14%
Anxiety | 4% | 3%
Anorexia | 4% | 2%
Agitation | 3% | 1%
Dysmenorrhea^1 | 3% | 2%
Libido Decreased | 2% | <1%
Yawning | 2% | <1%
Respiratory System Disorders
Upper Respiratory Tract Infection | 5% | 4%
Rhinitis | 5% | 3%
Sinusitis | 3% | <1%
Urogenital
Ejaculation Disorder^2,3 | 6% | 1%
Impotence^3 | 3% | <1%

*Events reported by at least 2% of patients treated with Celexa are reported, except for the following events which had an incidence on placebo > Celexa: headache, asthenia, dizziness, constipation, palpitation, vision abnormal, sleep disorder, nervousness, pharyngitis, micturition disorder, back pain.
^1Denominator used was for females only (N=638 Celexa; N=252 placebo).
^2Primarily ejaculatory delay.
^3Denominator used was for males only (N=425 Celexa; N=194 placebo).

Dose Dependency of Adverse Events

The potential relationship between the dose of Celexa administered and the incidence of adverse events was examined in a fixed-dose study in depressed patients receiving placebo or Celexa 10, 20, 40, and 60 mg. Jonckheere's trend test revealed a positive dose response (p<0.05) for the following adverse events: fatigue, impotence, insomnia, sweating increased, somnolence, and yawning.

Male and Female Sexual Dysfunction with SSRIs

Although changes in sexual desire, sexual performance, and sexual satisfaction often occur as manifestations of a psychiatric disorder, they may also be a consequence of pharmacologic treatment. In particular, some evidence suggests that SSRIs can cause such untoward sexual experiences.

Reliable estimates of the incidence and severity of untoward experiences involving sexual desire, performance, and satisfaction are difficult to obtain, however, in part because patients and physicians may be reluctant to discuss them. Accordingly, estimates of the incidence of untoward sexual experience and performance cited in product labeling, are likely to underestimate their actual incidence.

The table below displays the incidence of sexual side effects reported by at least 2% of patients taking Celexa in a pool of placebo-controlled clinical trials in patients with depression.

Treatment | Celexa (425 males) | Placebo (194 males)
Abnormal Ejaculation (mostly ejaculatory delay) | 6.1% (males only) | 1% (males only)
Libido Decreased | 3.8% (males only) | <1% (males only)
Impotence | 2.8% (males only) | <1% (males only)

In female depressed patients receiving Celexa, the reported incidence of decreased libido and anorgasmia was 1.3% (n=638 females) and 1.1% (n=252 females), respectively.

There are no adequately designed studies examining sexual dysfunction with citalopram treatment.

Priapism has been reported with all SSRIs.

While it is difficult to know the precise risk of sexual dysfunction associated with the use of SSRIs, physicians should routinely inquire about such possible side effects.

Vital Sign Changes

Celexa and placebo groups were compared with respect to (1) mean change from baseline in vital signs (pulse, systolic blood pressure, and diastolic blood pressure) and (2) the incidence of patients meeting criteria for potentially clinically significant changes from baseline in these variables. These analyses did not reveal any clinically important changes in vital signs associated with Celexa treatment. In addition, a comparison of supine and standing vital sign measures for Celexa and placebo treatments indicated that Celexa treatment is not associated with orthostatic changes.

Weight Changes

Patients treated with Celexa in controlled trials experienced a weight loss of about 0.5 kg compared to no change for placebo patients.

Laboratory Changes

Celexa and placebo groups were compared with respect to (1) mean change from baseline in various serum chemistry, hematology, and urinalysis variables, and (2) the incidence of patients meeting criteria for potentially clinically significant changes from baseline in these variables. These analyses revealed no clinically important changes in laboratory test parameters associated with Celexa treatment.

ECG Changes

Electrocardiograms from Celexa (N=802) and placebo (N=241) groups were compared with respect to (1) mean change from baseline in various ECG parameters, and (2) the incidence of patients meeting criteria for potentially clinically significant changes from baseline in these variables. The only statistically significant drug-placebo difference observed was a decrease in heart rate for Celexa of 1.7 bpm compared to no change in heart rate for placebo. There were no observed differences in QT or other ECG intervals.

Other Events Observed During the Premarketing Evaluation of Celexa (citalopram HBr)

Following is a list of WHO terms that reflect treatment-emergent adverse events, as defined in the introduction to the ADVERSE REACTIONS section, reported by patients treated with Celexa at multiple doses in a range of 10 to 80 mg/day during any phase of a trial within the premarketing database of 4422 patients. All reported events are included except those already listed in Table 3 or elsewhere in labeling, those events for which a drug cause was remote, those event terms which were so general as to be uninformative, and those occurring in only one patient. It is important to emphasize that, although the events reported occurred during treatment with Celexa, they were not necessarily caused by it.

Events are further categorized by body system and listed in order of decreasing frequency according to the following definitions: frequent adverse events are those occurring on one or more occasions in at least 1/100 patients; infrequent adverse events are those occurring in less than 1/100 patients but at least 1/1000 patients; rare events are those occurring in fewer than 1/1000 patients.

Cardiovascular - Frequent: tachycardia, postural hypotension, hypotension. Infrequent: hypertension, bradycardia, edema (extremities), angina pectoris, extrasystoles, cardiac failure, flushing, myocardial infarction, cerebrovascular accident, myocardial ischemia. Rare: transient ischemic attack, phlebitis, atrial fibrillation, cardiac arrest, bundle branch block.

Central and Peripheral Nervous System Disorders - Frequent: paresthesia, migraine. Infrequent: hyperkinesia, vertigo, hypertonia, extrapyramidal disorder, leg cramps, involuntary muscle contractions, hypokinesia, neuralgia, dystonia, abnormal gait, hypesthesia, ataxia. Rare: abnormal coordination, hyperesthesia, ptosis, stupor.

Endocrine Disorders - Rare: hypothyroidism, goiter, gynecomastia.

Gastrointestinal Disorders - Frequent: saliva increased, flatulence. Infrequent: gastritis, gastroenteritis, stomatitis, eructation, hemorrhoids, dysphagia, teeth grinding, gingivitis, esophagitis. Rare: colitis, gastric ulcer, cholecystitis, cholelithiasis, duodenal ulcer, gastroesophageal reflux, glossitis, jaundice, diverticulitis, rectal hemorrhage, hiccups.

General - Infrequent: hot flushes, rigors, alcohol intolerance, syncope, influenza-like symptoms. Rare: hayfever.

Hemic and Lymphatic Disorders - Infrequent: purpura, anemia, epistaxis, leukocytosis, leucopenia, lymphadenopathy. Rare: pulmonary embolism, granulocytopenia, lymphocytosis, lymphopenia, hypochromic anemia, coagulation disorder, gingival bleeding.

Metabolic and Nutritional Disorders - Frequent: decreased weight, increased weight. Infrequent: increased hepatic enzymes, thirst, dry eyes, increased alkaline phosphatase, abnormal glucose tolerance. Rare: bilirubinemia, hypokalemia, obesity, hypoglycemia, hepatitis, dehydration.

Musculoskeletal System Disorders - Infrequent: arthritis, muscle weakness, skeletal pain. Rare: bursitis, osteoporosis.

Psychiatric Disorders - Frequent: impaired concentration, amnesia, apathy, depression, increased appetite, aggravated depression, suicide attempt, confusion. Infrequent: increased libido, aggressive reaction, paroniria, drug dependence, depersonalization, hallucination, euphoria, psychotic depression, delusion, paranoid reaction, emotional lability, panic reaction, psychosis. Rare: catatonic reaction, melancholia.

Reproductive Disorders/Female* - Frequent: amenorrhea. Infrequent: galactorrhea, breast pain, breast enlargement, vaginal hemorrhage.

*% based on female subjects only: 2955

Respiratory System Disorders - Frequent: coughing. Infrequent: bronchitis, dyspnea, pneumonia. Rare: asthma, laryngitis, bronchospasm, pneumonitis, sputum increased.

Skin and Appendages Disorders - Frequent: rash, pruritus. Infrequent: photosensitivity reaction, urticaria, acne, skin discoloration, eczema, alopecia, dermatitis, skin dry, psoriasis. Rare: hypertrichosis, decreased sweating, melanosis, keratitis, cellulitis, pruritus ani.

Special Senses - Frequent: accommodation abnormal, taste perversion. Infrequent: tinnitus, conjunctivitis, eye pain. Rare: mydriasis, photophobia, diplopia, abnormal lacrimation, cataract, taste loss.

Urinary System Disorders - Frequent: polyuria. Infrequent: micturition frequency, urinary incontinence, urinary retention, dysuria. Rare: facial edema, hematuria, oliguria, pyelonephritis, renal calculus, renal pain.

Other Events Observed During the Postmarketing Evaluation of Celexa (citalopram HBr)

It is estimated that over 30 million patients have been treated with Celexa since market introduction. Although no causal relationship to Celexa treatment has been found, the following adverse events have been reported to be temporally associated with Celexa treatment, and have not been described elsewhere in labeling: acute renal failure, akathisia, allergic reaction, anaphylaxis, angioedema, choreoathetosis, chest pain, delirium, dyskinesia, ecchymosis, epidermal necrolysis, erythema multiforme, gastrointestinal hemorrhage, glaucoma, grand mal convulsions, hemolytic anemia, hepatic necrosis, myoclonus, nystagmus, pancreatitis, priapism, prolactinemia, prothrombin decreased, QT prolonged, rhabdomyolysis, spontaneous abortion, thrombocytopenia, thrombosis, ventricular arrhythmia, torsade de pointes, and withdrawal syndrome.

DRUG ABUSE AND DEPENDENCE

Controlled Substance Class

Celexa (citalopram HBr) is not a controlled substance.

Physical and Psychological Dependence

Animal studies suggest that the abuse liability of Celexa is low. Celexa has not been systematically studied in humans for its potential for abuse, tolerance, or physical dependence. The premarketing clinical experience with Celexa did not reveal any drug-seeking behavior. However, these observations were not systematic and it is not possible to predict, on the basis of this limited experience, the extent to which a CNS-active drug will be misused, diverted, and/or abused once marketed. Consequently, physicians should carefully evaluate Celexa patients for history of drug abuse and

OVERDOSAGE

Human Experience

In clinical trials of citalopram, there were reports of citalopram overdose, including overdoses of up to 2000mg, with no associated fatalities. During the postmarketing evaluation of citalopram, Celexa overdoses, including overdoses of up to 6000 mg, have been reported. As with other SSRI's, a fatal outcome in a patient who has taken an overdose of citalopram has been rarely reported.

Symptoms most often accompanying citalopram overdose, alone or in combination with other drugs and/or alcohol, included dizziness, sweating, nausea, vomiting, tremor, somnolence, and sinus tachycardia. In more rare cases, observed symptoms included amnesia, confusion, coma, convulsions, hyperventilation, cyanosis, rhabdomyolysis, and ECG changes (including QTc prolongation, nodal rhythm, ventricular arrhythmia, and very rare cases of torsade de pointes). Acute renal failure has been very rarely reported accompanying overdose.

Management of Overdose

Establish and maintain an airway to ensure adequate ventilation and oxygenation. Gastric evacuation by lavage and use of activated charcoal should be considered. Careful observation and cardiac and vital sign monitoring are recommended, along with general symptomatic and supportive care. Due to the large volume of distribution of citalopram, forced diuresis, dialysis, hemoperfusion, and exchange transfusion are unlikely to be of benefit. There are no specific antidotes for Celexa.

In managing overdosage, consider the possibility of multiple-drug involvement. The physician should consider contacting a poison control center for additional information on the treatment of any overdose.

DOSAGE AND ADMINISTRATION

Initial Treatment

Celexa (citalopram HBr) should be administered at an initial dose of 20 mg once daily, generally with an increase to a dose of 40 mg/day. Dose increases should usually occur in increments of 20 mg at intervals of no less than one week. Although certain patients may require a dose of 60 mg/day, the only study pertinent to dose response for effectiveness did not demonstrate an advantage for the 60 mg/day dose over the 40 mg/day dose; doses above 40 mg are therefore not ordinarily recommended.

Celexa should be administered once daily, in the morning or evening, with or without food.

Special Populations

20 mg/day is the recommended dose for most elderly patients and patients with hepatic impairment, with titration to 40 mg/day only for nonresponding patients.

No dosage adjustment is necessary for patients with mild or moderate renal impairment. Celexa should be used with caution in patients with severe renal impairment.

Treatment of Pregnant Women During the Third Trimester

Neonates exposed to Celexa and other SSRIs or SNRIs, late in the third trimester, have developed complications requiring prolonged hospitalization, respiratory support, and tube feeding (see PRECAUTIONS). When treating pregnant women with Celexa during the third trimester, the physician should carefully consider the potential risks and benefits of treatment. The physician may consider tapering Celexa in the third trimester.

Maintenance Treatment

It is generally agreed that acute episodes of depression require several months or longer of sustained pharmacologic therapy. Systematic evaluation of Celexa in two studies has shown that its antidepressant efficacy is maintained for periods of up to 24 weeks following 6 or 8 weeks of initial treatment (32 weeks total). In one study, patients were assigned randomly to placebo or to the same dose of Celexa (20-60 mg/day) during maintenance treatment as they had received during the acute stabilization phase, while in the other study, patients were assigned randomly to continuation of Celexa 20 or 40 mg/day, or placebo, for maintenance treatment. In the latter study, the rates of relapse to depression were similar for the two dose groups (see Clinical Trials under CLINICAL PHARMACOLOGY). Based on these limited data, it is not known whether the dose of citalopram needed to maintain euthymia is identical to the dose needed to induce remission. If adverse reactions are bothersome, a decrease in dose to 20 mg/day can be considered.

Discontinuation of Treatment with Celexa

Symptoms associated with discontinuation of Celexa and other SSRIs and SNRIs have been reported (see PRECAUTIONS). Patients should be monitored for these symptoms when discontinuing treatment. A gradual reduction in the dose rather than abrupt cessation is recommended whenever possible. If intolerable symptoms occur following a decrease in the dose or upon discontinuation of treatment, then resuming the previously prescribed dose may be considered. Subsequently, the physician may continue decreasing the dose but at a more gradual rate.

Switching Patients To or From a Monoamine Oxidase Inhibitor

At least 14 days should elapse between discontinuation of an MAOI and initiation of Celexa therapy. Similarly, at least 14 days should be allowed after stopping Celexa before starting an MAOI (see CONTRAINDICATIONS and WARNINGS).

HOW SUPPLIED

Tablets:

10 mg Beige, oval, film-coated. Imprint on one side with "FP". Imprint on the other side with "10 mg".

Bottles of 10 | NDC 54868-4985-1
Bottles of 30 | NDC 54868-4985-0

20 mg Pink, oval, scored, film-coated. Imprint on scored side with "F" on the left side and "P" on the right side. Imprint on the non-scored side with "20 mg".

Bottles of 10 | NDC 54868-4159-1
Bottles of 15 | NDC 54868-4159-3
Bottles of 30 | NDC 54868-4159-0
Bottles of 90 | NDC 54868-4159-2
Bottles of 100 | NDC 54868-4159-4

40 mg White, oval, scored, film-coated. Imprint on scored side with "F" on the left side and "P" on the right side. Imprint on the non-scored side with "40 mg".

Bottles of 10 | NDC 54868-4226-1
Bottles of 30 | NDC 54868-4226-0
Bottles of 50 | NDC 54868-4226-2

ANIMAL TOXICOLOGY

Retinal Changes in Rats

Pathologic changes (degeneration/atrophy) were observed in the retinas of albino rats in the 2-year carcinogenicity study with citalopram. There was an increase in both incidence and severity of retinal pathology in both male and female rats receiving 80 mg/kg/day (13 times the maximum recommended daily human dose of 60 mg on a mg/m^2 basis). Similar findings were not present in rats receiving 24 mg/kg/day for two years, in mice treated for 18 months at doses up to 240 mg/kg/day, or in dogs treated for one year at doses up to 20 mg/kg/day (4, 20, and 10 times, respectively, the maximum recommended daily human dose on a mg/m^2 basis).

Additional studies to investigate the mechanism for this pathology have not been performed, and the potential significance of this effect in humans has not been established.

Cardiovascular Changes in Dogs

In a one-year toxicology study, 5 of 10 beagle dogs receiving oral doses of 8 mg/kg/day (4 times the maximum recommended daily human dose of 60 mg on a mg/m^2 basis) died suddenly between weeks 17 and 31 following initiation of treatment. Although appropriate data from that study are not available to directly compare plasma levels of citalopram (CT) and its metabolites, demethylcitalopram (DCT) and didemethylcitalopram (DDCT), to levels that have been achieved in humans, pharmacokinetic data indicate that the relative dog-to-human exposure was greater for the metabolites than for citalopram. Sudden deaths were not observed in rats at doses up to 120 mg/kg/day, which produced plasma levels of CT, DCT, and DDCT similar to those observed in dogs at doses of 8 mg/kg/day. A subsequent intravenous dosing study demonstrated that in beagle dogs, DDCT caused QT prolongation, a known risk factor for the observed outcome in dogs. This effect occurred in dogs at doses producing peak DDCT plasma levels of 810 to 3250 nM (39-155 times the mean steady state DDCT plasma level measured at the maximum recommended human daily dose of 60 mg). In dogs, peak DDCT plasma concentrations are approximately equal to peak CT plasma concentrations, whereas in humans, steady state DDCT plasma concentrations are less than 10% of steady state CT plasma concentrations. Assays of DDCT plasma concentrations in 2020 citalopram-treated individuals demonstrated that DDCT levels rarely exceeded 70 nM; the highest measured level of DDCT in human overdose was 138 nM. While DDCT is ordinarily present in humans at lower levels than in dogs, it is unknown whether there are individuals who may achieve higher DDCT levels. The possibility that DCT, a principal metabolite in humans, may prolong the QT interval in dogs has not been directly examined because DCT is rapidly converted to DDCT in that species.

Forest Pharmaceuticals, Inc.
Subsidiary of Forest Laboratories, Inc.
St. Louis, MO 63045 USA

Licensed from H. Lundbeck A/S

Rev. 01/09

© 2009 Forest Laboratories, Inc.

Relabeling and Repackaging by:
Physicians Total Care, Inc.
Tulsa, OK 74146

Medication Guide

Antidepressant Medicines, Depression and other Serious Mental Illnesses, and Suicidal Thoughts or Actions

Read the Medication Guide that comes with you or your family member's antidepressant medicine. This Medication Guide is only about the risk of suicidal thoughts and actions with antidepressant medicines. Talk to your, or your family member's, healthcare provider about:

- all risks and benefits of treatment with antidepressant medicines
- all treatment choices for depression or other serious mental illness

What is the most important information I should know about antidepressant medicines, depression and other serious mental illnesses, and suicidal thoughts or actions?

1. 1. Antidepressant medicines may increase suicidal thoughts or actions in some children, teenagers, and young adults within the first few months of treatment.
2. Depression and other serious mental illnesses are the most important causes of suicidal thoughts and actions. Some people may have a particularly high risk of having suicidal thoughts or actions. These include people who have (or have a family history of) bipolar illness (also called manic-depressive illness) or suicidal thoughts or actions.
3. How can I watch for and try to prevent suicidal thoughts and actions in myself or a family member?
  - Pay close attention to any changes, especially sudden changes, in mood, behaviors, thoughts, or feelings. This is very important when an antidepressant medicine is started or when the dose is changed.
  - Call the healthcare provider right away to report new or sudden changes in mood, behavior, thoughts, or feelings.
  - Keep all follow-up visits with the healthcare provider as scheduled. Call the healthcare provider between visits as needed, especially if you have concerns about symptoms.

Call a healthcare provider right away if you or your family member has any of the following symptoms, especially if they are new, worse, or worry you:

- thoughts about suicide or dying
- attempts to commit suicide
- new or worse depression
- new or worse anxiety
- feeling very agitated or restless
- panic attacks
- trouble sleeping (insomnia)
- new or worse irritability
- acting aggressive, being angry, or violent
- acting on dangerous impulses
- an extreme increase in activity and talking
  (mania)
- other unusual changes in behavior or mood

Call your doctor for medical advice about side effects. You may report side effects to FDA at 1-800-FDA-1088

What else do I need to know about antidepressant medicines?

- Never stop an antidepressant medicine without first talking to a healthcare provider. Stopping an antidepressant medicine suddenly can cause other symptoms.
- Antidepressants are medicines used to treat depression and other illnesses. It is important to discuss all the risks of treating depression and also the risks of not treating it. Patients and their families or other caregivers should discuss all treatment choices with the healthcare provider, not just the use of antidepressants.
- Antidepressant medicines have other side effects. Talk to the healthcare provider about the side effects of the medicine prescribed for you or your family member.
- Antidepressant medicines can interact with other medicines. Know all of the medicines that you or your family member takes. Keep a list of all medicines to show the healthcare provider. Do not start new medicines without first checking with your healthcare provider.
- Not all antidepressant medicines prescribed for children are FDA approved for use in children. Talk to your child's healthcare provider for more information.

This Medication Guide has been approved by the U.S. Food and Drug Administration for all antidepressants.

Rev. 01/09

PRINCIPAL DISPLAY PANEL

Celexa® (citalopram HBr)

10 mg tablets

20 mg tablets

40 mg tablets